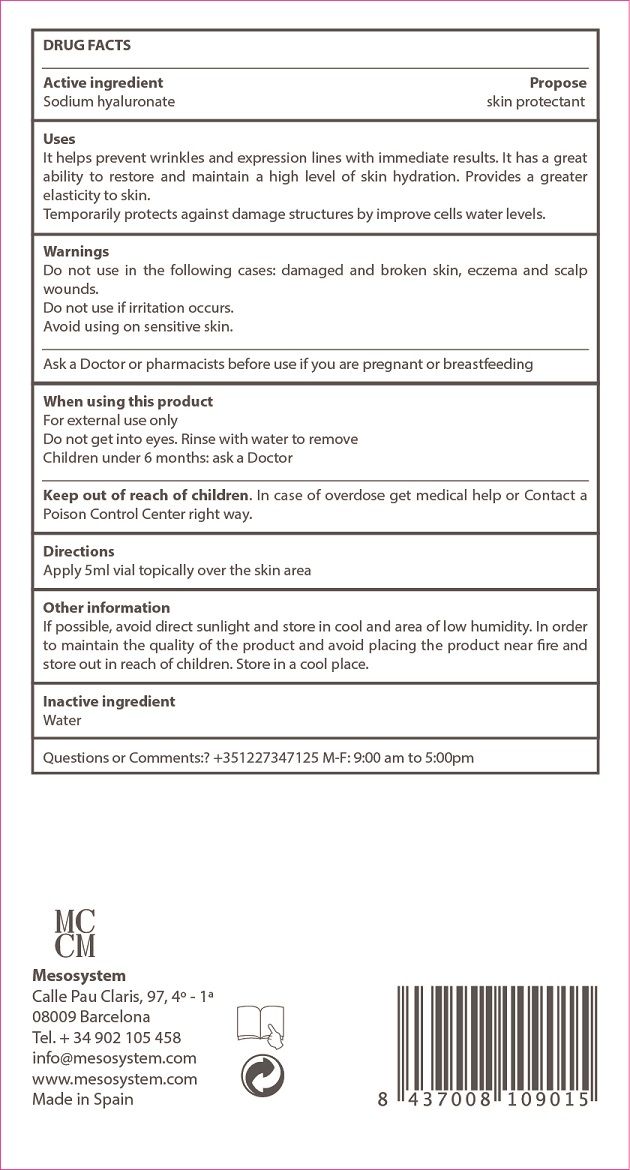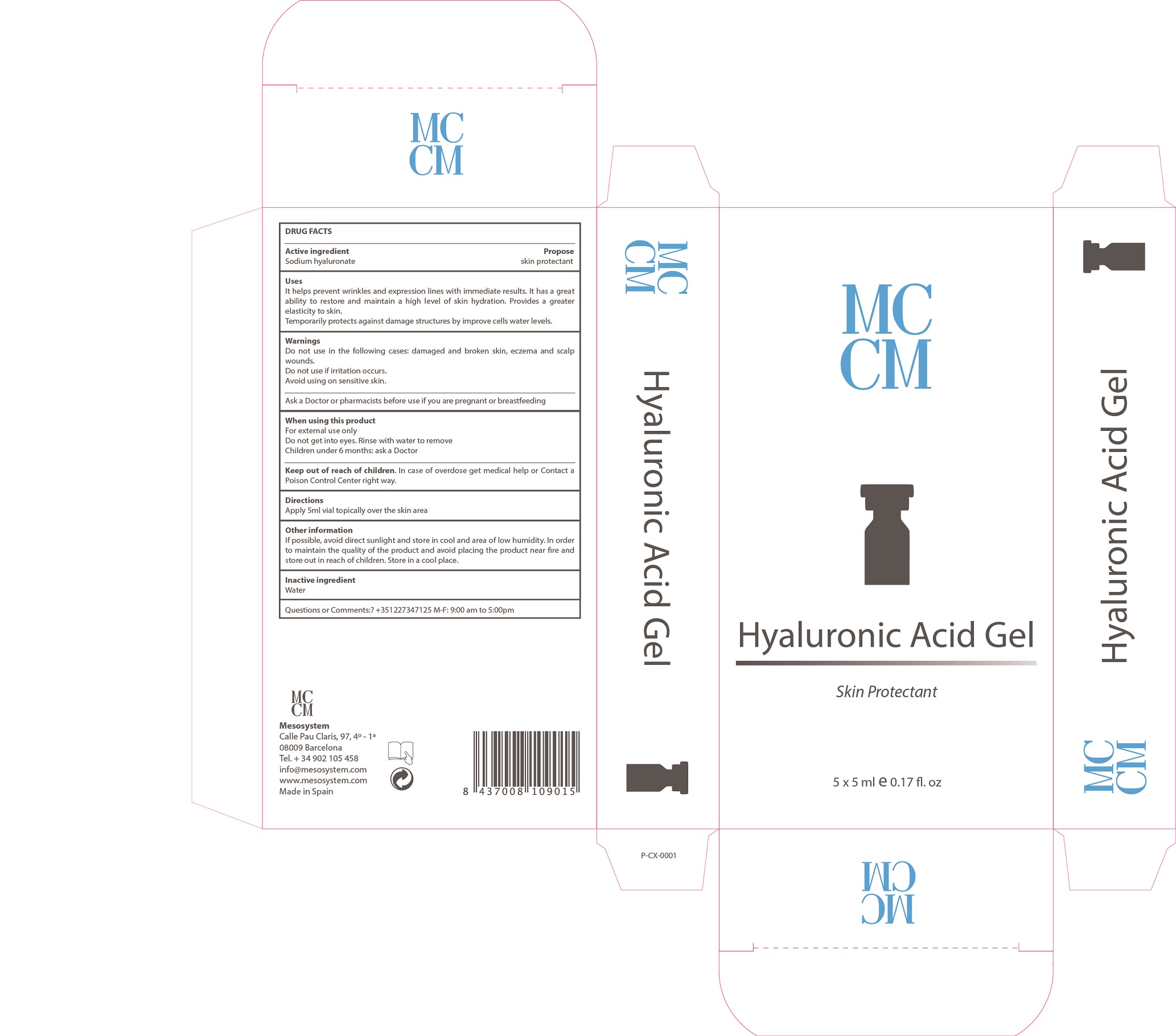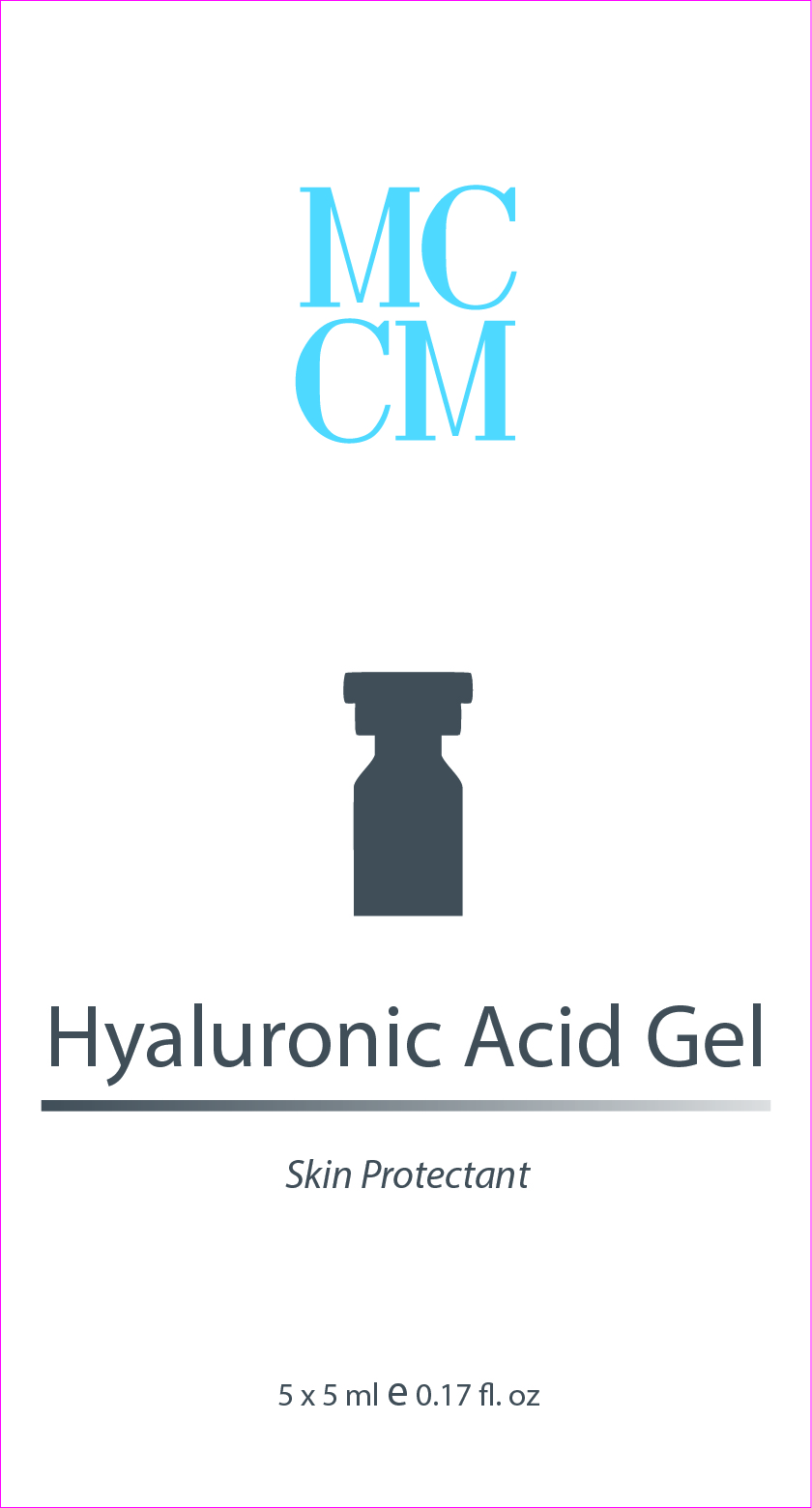 DRUG LABEL: Hyaluronic Acid Gel
NDC: 70663-005 | Form: GEL
Manufacturer: Meso System S.A.
Category: otc | Type: HUMAN OTC DRUG LABEL
Date: 20161214

ACTIVE INGREDIENTS: HYALURONATE SODIUM 3.5 mg/1 mL
INACTIVE INGREDIENTS: WATER 96.5 mg/1 mL

Hyaluronic Acid Gel

Uses

helps to prevent wrinkles and expression lines with inmediate results. It has a great ability to restore and maintain a high level of skin hydration. Provides a greater elasticity to skin.

. temporarily protects against damage structures by improving cells water levels.

Warnings

For external use only.

Do not use on the following cases: damaged or broken skin, eczema and scalp wounds.

Do not use if irritation occurs

Avoid using on sensitive skins.

When using this product keep our of the eyes. Rinse with water to remove.

Keep out of reach of children.

Children under 6 months: as a doctor.

Keep out of reach of children.

Warnings

Stop use and ask a doctor if rash occurs.

Questions or comments?

+ (35) 122 7347 125 M-F 9:00 am to 5:00 pm

Directions

. apply 5 ml vial topically over the skin areas

Other information

. if possible, avoid direct sunlight and stores in a cool area of low humidity. In order to maintain the quality of the product, avoid placing the product near fire and store out of the reach of children.

. store in a cool place

Inactive ingredients

water

Directions

. apply 5ml vial topically on the skin areas

Active Ingredients Purpose

Active Ingredient Purpose

Sodium Hyaluronate.................... Skin Protectant

Uses

. helps to prevent wrinkles and expression lines with inmediate results. It has a great ability to restore and maintain a high level of skin hydration. Provides a greater elasticity to skin.

. temporarily protects against damage structures by improving cells water levels.

Principal Display Panel

Hyaluronic Acid Gel

Skin Protectant

Hyaluronic Acid Gel

Skin Protectant